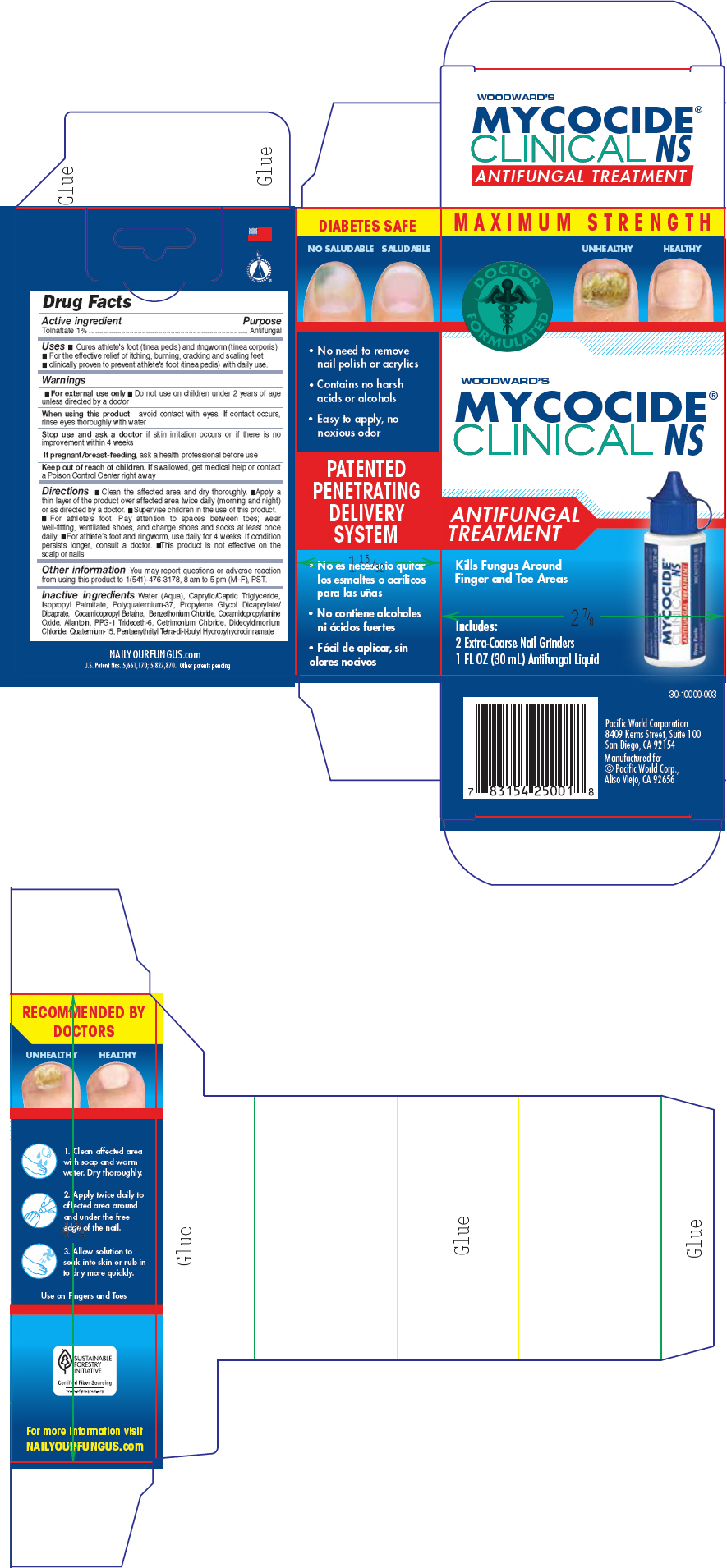 DRUG LABEL: Woodwards Mycocide Clinical NS
NDC: 60193-100 | Form: LIQUID
Manufacturer: Pacific World Corporation
Category: otc | Type: HUMAN OTC DRUG LABEL
Date: 20141020

ACTIVE INGREDIENTS: TOLNAFTATE 10 mg/1 mL
INACTIVE INGREDIENTS: WATER; MEDIUM-CHAIN TRIGLYCERIDES; ISOPROPYL PALMITATE; POLYQUATERNIUM-37 (3000 MPA.S); PROPYLENE GLYCOL DICAPRYLATE/DICAPRATE; COCAMIDOPROPYL BETAINE; BENZETHONIUM CHLORIDE; COCAMIDOPROPYLAMINE OXIDE; ALLANTOIN; PPG-1 TRIDECETH-6; CETRIMONIUM CHLORIDE; DIDECYLDIMONIUM CHLORIDE; QUATERNIUM-15; PENTAERYTHRITOL TETRAKIS(3-(3,5-DI-TERT-BUTYL-4-HYDROXYPHENYL)PROPIONATE)

Woodward's Mycocide Clinical NS

Active ingredient

Tolnaftate 1%

Purpose

Antifungal

Uses

- Cures most fungal skin infections, including athlete's foot (tinea pedis) and ringworm (tinea corporis)
- Effectively relieves itching, burning, cracking and scaling accompanying such conditions

Warnings

For external use only.

Do not use

- near the mouth or eyes
- with known sensitivities to any listed ingredients
- on children under 2 years of age unless directed by a doctor

When using this product avoid eye contact. If accidental eye contact occurs, rinse thoroughly with water for 10-15 minutes.

STOP USE

Stop use and ask a doctor if rash or irritation occurs, or if no improvement is seen after four weeks.

PREGNANCY OR BREAST FEEDING

If pregnant/breast-feeding, consult a health professional before using.

Keep out of reach of children. If swallowed, get medical help or contact a Poison Control Center immediately.

Directions

- Clean affected area with soap and warm water and dry thoroughly
- Apply a thin layer two times a day (mornings and evenings) to affected area especially the space between and around toes
- For athlete's foot, use daily for four weeks or as directed by a physician
- Allow solution to soak into skin or rub in to dry more quickly before putting on socks
- This product is not effective on scalp or nails.
- Following a proper foot hygiene regimen along with wearing well fitting, ventilated shoes and clean socks that are changed at least daily is helpful in preventing future infections

Other information

You may report questions or adverse reaction from using this product to 1(541)-476-3178, 8 am to 5 pm (M–F), PST.

Inactive ingredients

Water (Aqua), Caprylic/Capric Triglycerides, Isopropyl Palmitate, Polyquaternium 37, Propylene Glycol, Dicaprylate Dicaprate, PPG-1 Trideceth-6, Cocamidopropyl Betaine, Cocamidopropylamine Oxide, Phemerol Chloride, Cetrimonium Chloride, Allantoin, Didecyldimonium Chloride, Quaternium-15.

PRINCIPAL DISPLAY PANEL - 30 mL Bottle Carton

MAXIMUM STRENGTH

UNHEALTHY
HEALTHY

DOCTOR
FORMULATED

WOODWARD'S
MYCOCIDE®
CLINICAL NS

ANTIFUNGAL
TREATMENT

Kills Fungus Around
Finger and Toe Areas

Includes:
2 Extra-Coarse Nail Grinders
NET WT 1 FL OZ (30 mL) Antifungal Liquid